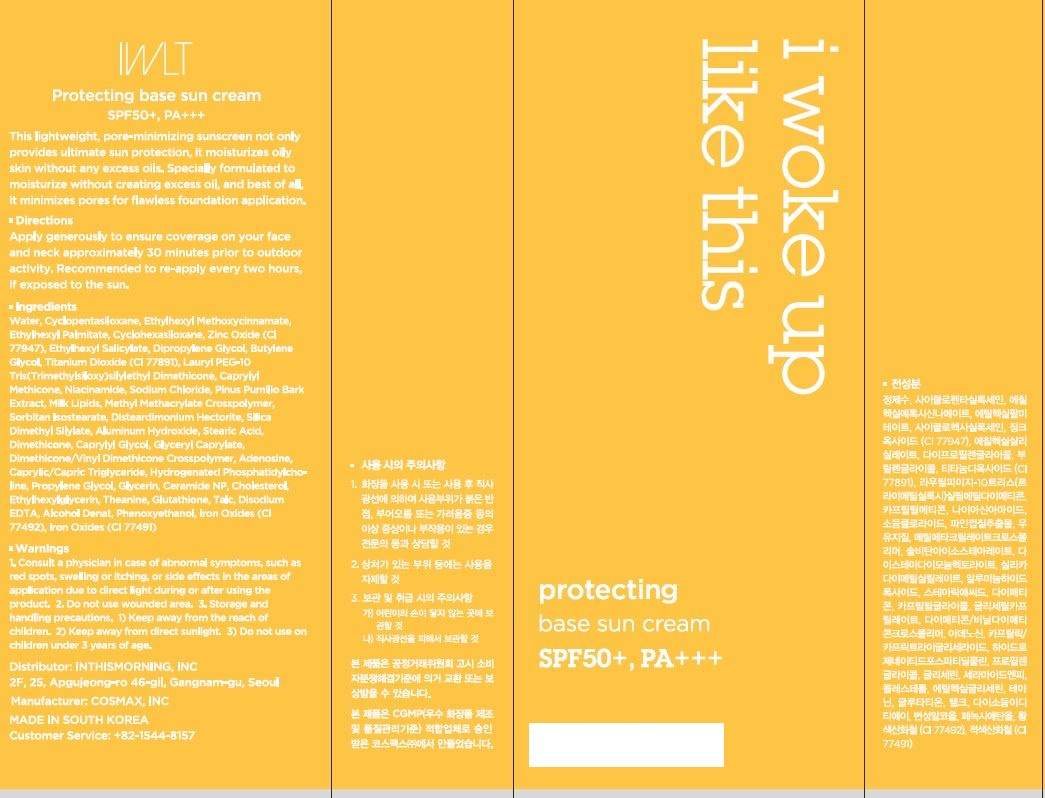 DRUG LABEL: Protecting base suncream
NDC: 71217-0060 | Form: CREAM
Manufacturer: inthismorning co ltd
Category: otc | Type: HUMAN OTC DRUG LABEL
Date: 20230130

ACTIVE INGREDIENTS: NIACINAMIDE 2 g/100 mL; ADENOSINE 0.04 g/100 mL
INACTIVE INGREDIENTS: WATER; GLYCERIN

Drug Facts

ACTIVE INGREDIENT

niacinamide, adenosine

INACTIVE INGREDIENT

Water
Cyclopentasiloxane
Ethylhexyl Methoxycinnamate
Ethylhexyl Palmitate
Cyclohexasiloxane
Zinc Oxide (CI 77947)
Ethylhexyl Salicylate
Dipropylene Glycol
Butylene Glycol
Titanium Dioxide (CI 77891)
Lauryl PEG-10 Tris(Trimethylsiloxy)silylethyl Dimethicone
Caprylyl Methicone
Sodium Chloride
Methyl Methacrylate Crosspolymer
Sorbitan Isostearate
Disteardimonium Hectorite
Silica Dimethyl Silylate
Aluminum Hydroxide
Stearic Acid
Dimethicone
Caprylyl Glycol
Glyceryl Caprylate
Dimethicone/Vinyl Dimethicone Crosspolymer
Iron Oxides (CI 77492)
Iron Oxides (CI 77491)
Talc
Disodium EDTA
Caprylic/Capric Triglyceride
Hydrogenated Phosphatidylcholine
Propylene Glycol
Alcohol Denat.
Glycerin
Ceramide NP
Cholesterol
Pinus Pumilio Bark Extract
Phenoxyethanol
Ethylhexylglycerin
Theanine
Milk Lipids
Glutathione

PURPOSE

brightening, wrinkle care

keep out or reach of the children

INDICATIONS AND USAGE

apply generously to ensure coverage on your face and neck approximately 30 minutes prior to outdoor activity

recommended to re-apply every two hours, if exposed to the sun

WARNINGS

This product is for exeternal use only. Do not use for internal use
Storage and handling precautions
If possible, avoid direct sunlight and store in cool and area of low humidity in order to maintain the quality of the product and avoid misuse
Avoid placing the product near fire and store out in reach of children

- consult a physician in case of abnormal symptoms, such as red spots, swelling or itching, or side effects in the areas of application due to direct light during or after using the product

- do not use on wounded area

DOSAGE AND ADMINISTRATION

for external use only